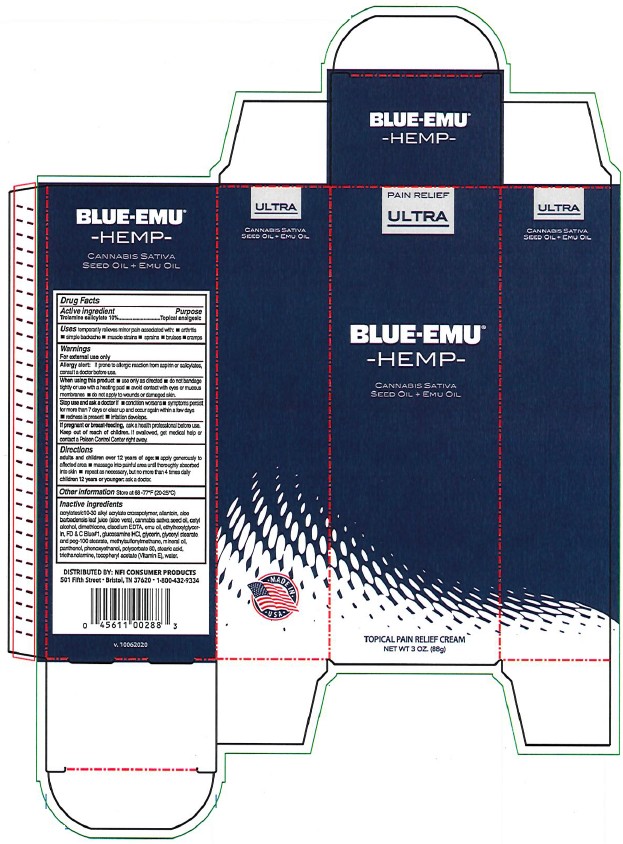 DRUG LABEL: Blue-Emu Ultra with Hemp Seed
NDC: 69993-200 | Form: CREAM
Manufacturer: Kingsway Pharmaceuticals dba NFI, LLC
Category: otc | Type: HUMAN OTC DRUG LABEL
Date: 20241220

ACTIVE INGREDIENTS: TROLAMINE SALICYLATE 0.1 g/1 g
INACTIVE INGREDIENTS: ALLANTOIN; ALOE VERA LEAF; CANNABIS SATIVA SEED OIL; CETYL ALCOHOL; DIMETHICONE, UNSPECIFIED; EDETATE DISODIUM ANHYDROUS; EMU OIL; ETHYLHEXYLGLYCERIN; FD&C BLUE NO. 1; GLUCOSAMINE HYDROCHLORIDE; GLYCERIN; GLYCERYL STEARATE/PEG-100 STEARATE; DIMETHYL SULFONE; MINERAL OIL; PANTHENOL; PHENOXYETHANOL; POLYSORBATE 80; STEARIC ACID; TROLAMINE; .ALPHA.-TOCOPHEROL; WATER

Blue-Emu® Ultra with Hemp Seed Oil

Active Ingredient

Trolamine salicylate 10%

Purpose

Topical analgesic

Uses

temporarily relieves minor pain associated with:

- arthritis
- simple backache
- muscle strains
- sprains
- bruises
- cramps

Warnings

For external use only

Allergy alert: If prone to allergic reaction from aspirin or salicylates, consult a doctor before use.

When using this product

- use only as directed
- do not bandage tightly or use with a heating pad
- avoid contact with eyes or mucous membranes
- do not apply to wounds or damaged skin.

Stop use and ask a doctor if

- condition worsens
- symptoms persist for more than 7 days or clear up and occur again within a few days
- redness is present
- irritation develops.

PREGNANCY OR BREAST FEEDING

If pregnant or breast-feeding, ask a health professional before use.

Keep out of reach of children. If swallowed, get medical help or contact a Poison Control Center right away.

Directions

adults and children over 12 years of age:

- apply generously to affected area
- massage into painful area until thoroughly absorbed into skin
- repeat as necessary, but no more than 4 times daily

children 12 years or younger: ask a doctor.

Other information

Store at 68-77°F (20-25°C)

Inactive ingredients

acrylates/c10-30 alkyl acrylate crosspolymer, allantoin, aloe barbadensis leaf juice (aloe vera), cannabis sativa seed oil, cetyl alcohol, dimethicone, disodium EDTA, emu oil, ethylhexylglycerin, FD & C Blue#1, glucosamine HCl, glycerin, glyceryl stearate and peg-100 stearate, methylsulfonylmethane, mineral oil, panthenol, phenoxyethanol, polysorbate 80, stearic acid, triethanolamine, tocopheryl acetate (Vitamin E), water.

DISTRIBUTED BY: NFI CONSUMER PRODUCTS
501 Fifth Street • Bristol, TN 37620 • 1-800-432-9334

PRINCIPAL DISPLAY PANEL – Carton Label

PAIN RELIEF
ULTRA

BLUE-EMU®
-HEMP-

CANNABIS SATIVA
SEED OIL + EMU OIL

TOPICAL PAIN RELIEF CREAM
NET WT 3 OZ. (88g)